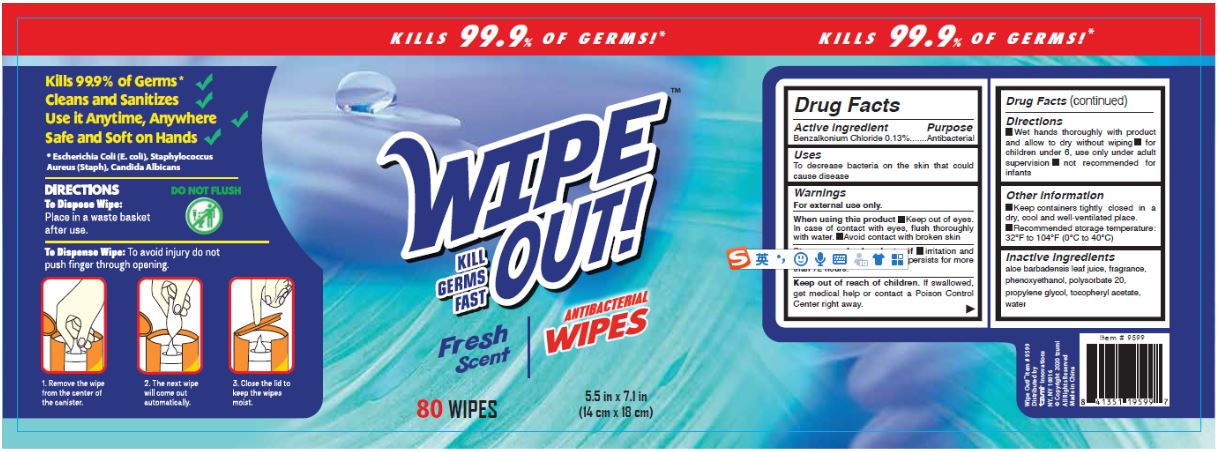 DRUG LABEL: Wipe-Out Antibacterial Wipes Fresh Scent
NDC: 79650-005 | Form: LIQUID
Manufacturer: Zhangzhou Zhongnan Nursing Products Co., Ltd.
Category: otc | Type: HUMAN OTC DRUG LABEL
Date: 20200810

ACTIVE INGREDIENTS: BENZALKONIUM CHLORIDE 0.13 mg/100 mL
INACTIVE INGREDIENTS: ALOE VERA LEAF; POLYSORBATE 20; WATER; PHENOXYETHANOL; PROPYLENE GLYCOL; ALPHA-TOCOPHEROL ACETATE

Active Ingredient

Benzalkonium Chloride 0.13%

Purpose

Antibacterial

Uses

To decrease bacteria on the skin that could cause disease

Warnings

For external use only.

When using this product

- Keep out of eyes. In case of contact with eyes, flush thoroughly with water.
- Avoid contact with broken skin

Stop use and ask a doctor if

- irritation and redness develop
- condition persists for more than 72 hours.

Keep out of reach of children. If swallowed, get medical help or contact a Poison Control Center right away.

Directions

- Wet hands thoroughly with product and allow to dry without wiping
- for children under 6, use only under adult supervision
- not recommended for infants

Other Information

- Keep containers tightly closed in a dry, cool and well-ventilated place.
- Recommended storage temperature: 32°F to 104°F (0°C to 40°C)

Inactive Ingredients

Aloe barbadensis leaf juice, fragrance, phenoxyethanol, polysorbate 20, propylene glycol, tocopheryl acetate, water

Package Label/Principal Display Panel

NDC 79650-005-02; 320 mL